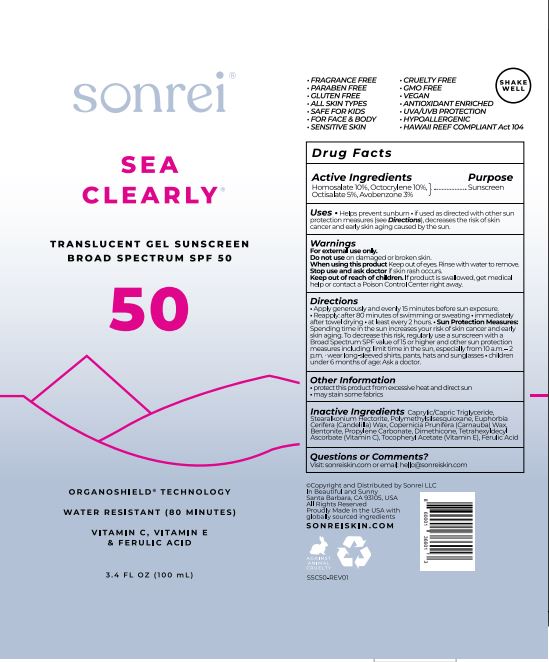 DRUG LABEL: Sea Clearly Translucent Gel Sunscreen BS SPF 50
NDC: 62742-4235 | Form: GEL
Manufacturer: Allure Labs
Category: otc | Type: HUMAN OTC DRUG LABEL
Date: 20231204

ACTIVE INGREDIENTS: HOMOSALATE 10 g/100 g; AVOBENZONE 3 g/100 g; OCTISALATE 5 g/100 g; OCTOCRYLENE 10 g/100 g
INACTIVE INGREDIENTS: PROPYLENE CARBONATE; DIMETHICONE; POLYMETHYLSILSESQUIOXANE/TRIMETHYLSILOXYSILICATE; CANDELILLA WAX; BENTONITE; TETRAHEXYLDECYL ASCORBATE; FERULIC ACID; MEDIUM-CHAIN TRIGLYCERIDES; .ALPHA.-TOCOPHEROL ACETATE; CARNAUBA WAX; STEARALKONIUM HECTORITE

Drug Facts

Active ingredient,

Homosalate – 10 %

Octocrylene – 10 %

Octisalate - 5%

Avobenzone – 3%

Purpose.

Sunscreen

INDICATIONS AND USAGE

Uses. Helps prevent sunburn.

If used as directed with other sun protection measures (see Direction), decreases the risk of skin cancer and early skin aging caused by the sun.

Warnings- For external use only.

Do not use on damaged or broken skin.

When using this product keep out of eye.Rinse with water to remove.

Stop use and ask doctor if skin rash occurs.

Keep out of reach of children, If product is swallowed, get medical help or contact a poison control center right away.

Directions.

Apply generously and evenly 15 minutes before sun exposure.

Reapply: after 80 minutes of swimming or sweating.

Immediately after towel drying. At least every 2 hours. Sun Protection Measures: Spending time the sun increases your risk of skin cancer and early skin aging. To decrease this risk, regularly use of sunscreen with a broad spectrum SPF value of 15 or higher and other sun protection measures including: limit time in the sun, especially from 10 a.m. – 2 p.m. wear long-sleeved shirts, pants, hats and sunglasses. Children under 6 months of age: Ask a doctor.

Other information.

Protect this product from excessive heat an direct sun.

May stain some fabrics.

Inactive ingredient:

Caprylic/Capric Triglyceride, Stearalkonium Hectorite, Polymethylsilsesquioxane, Euphorbia Cerifera (Candelilla) Wax, Copernicia Prunifera (Carnauba) Wax, Bentonite, Propylene Carbonate, Dimethicone, Tetrahexyldecyl Ascorbate (Vitamin C), Tocopheryl Acetate (Vitamin E), Ferulic Acid.